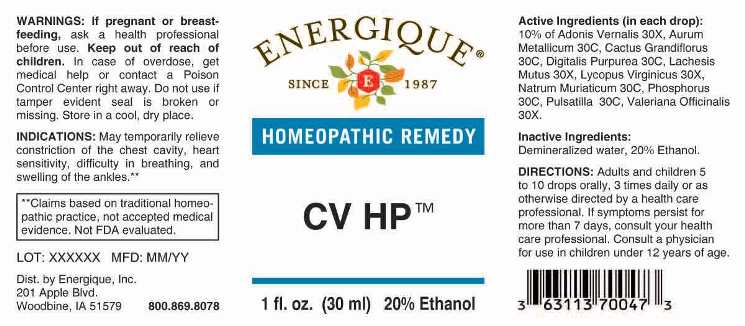 DRUG LABEL: CV
NDC: 44911-0196 | Form: LIQUID
Manufacturer: ENERGIQUE, INC.
Category: homeopathic | Type: HUMAN OTC DRUG LABEL
Date: 20241024

ACTIVE INGREDIENTS: ADONIS VERNALIS WHOLE 30 [hp_X]/1 mL; LACHESIS MUTA VENOM 30 [hp_X]/1 mL; LYCOPUS VIRGINICUS WHOLE 30 [hp_X]/1 mL; VALERIAN 30 [hp_X]/1 mL; GOLD 30 [hp_C]/1 mL; SELENICEREUS GRANDIFLORUS STEM 30 [hp_C]/1 mL; DIGITALIS 30 [hp_C]/1 mL; SODIUM CHLORIDE 30 [hp_C]/1 mL; PHOSPHORUS 30 [hp_C]/1 mL; PULSATILLA PRATENSIS 30 [hp_C]/1 mL
INACTIVE INGREDIENTS: WATER; ALCOHOL

DRUG FACTS:

ACTIVE INGREDIENTS:

(in each drop): 10% of Adonis Vernalis 30X, Aurum Metallicum 30C, Cactus Grandiflorus 30C, Digitalis Purpurea 30C, Lachesis Mutus 30X, Lycopus Virginicus 30X, Natrum Muriaticum 30C, Phosphorus 30C, Pulsatilla (Pratensis) 30C, Valeriana Officinalis 30X.

INDICATIONS:

May temporarily relieve constriction of the chest cavity, heart sensitivity, difficulty in breathing, and swelling of the ankles.**

**Claims based on traditional homeopathic practice, not accepted medical evidence. Not FDA evaluated.

WARNINGS:

If pregnant or breast-feeding, ask a health professional before use.

Keep out of reach of children. In case of overdose, get medical help or contact a Poison Control Center right away.

Do not use if tamper evident seal is broken or missing. Store in a cool, dry place.

Keep out of reach of children. In case of overdose, get medical help or contact a Poison Control Center right away.

DIRECTIONS:

Adults and children 5 to 10 drops orally, 3 times daily or as otherwise directed by a health care professional. If symptoms persist for more than 7 days, consult your health care professional.

Consult a physician for use in children under 12 years of age.

INDICATIONS:

May temporarily relieve constriction of the chest cavity, heart sensitivity, difficulty in breathing, and swelling of the ankles.**

**Claims based on traditional homeopathic practice, not accepted medical evidence. Not FDA evaluated.

INACTIVE INGREDIENTS:

Demineralized water, 20% Ethanol.

QUESTIONS:

Dist. by Energique, Inc.

201 Apple Blvd

Woodbine, IA 51579 800.869.8078

PACKAGE LABEL DISPLAY:

ENERGIQUE

SINCE 1987

HOMEOPATHIC REMEDY

CV HP

1 fl. oz. (30 ml)